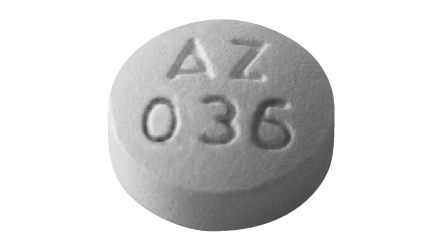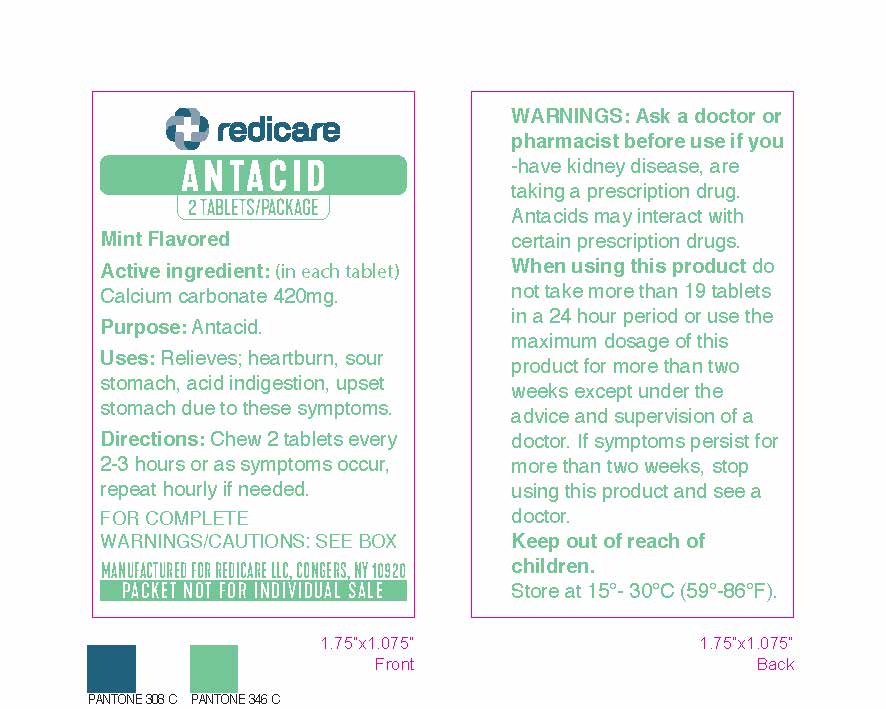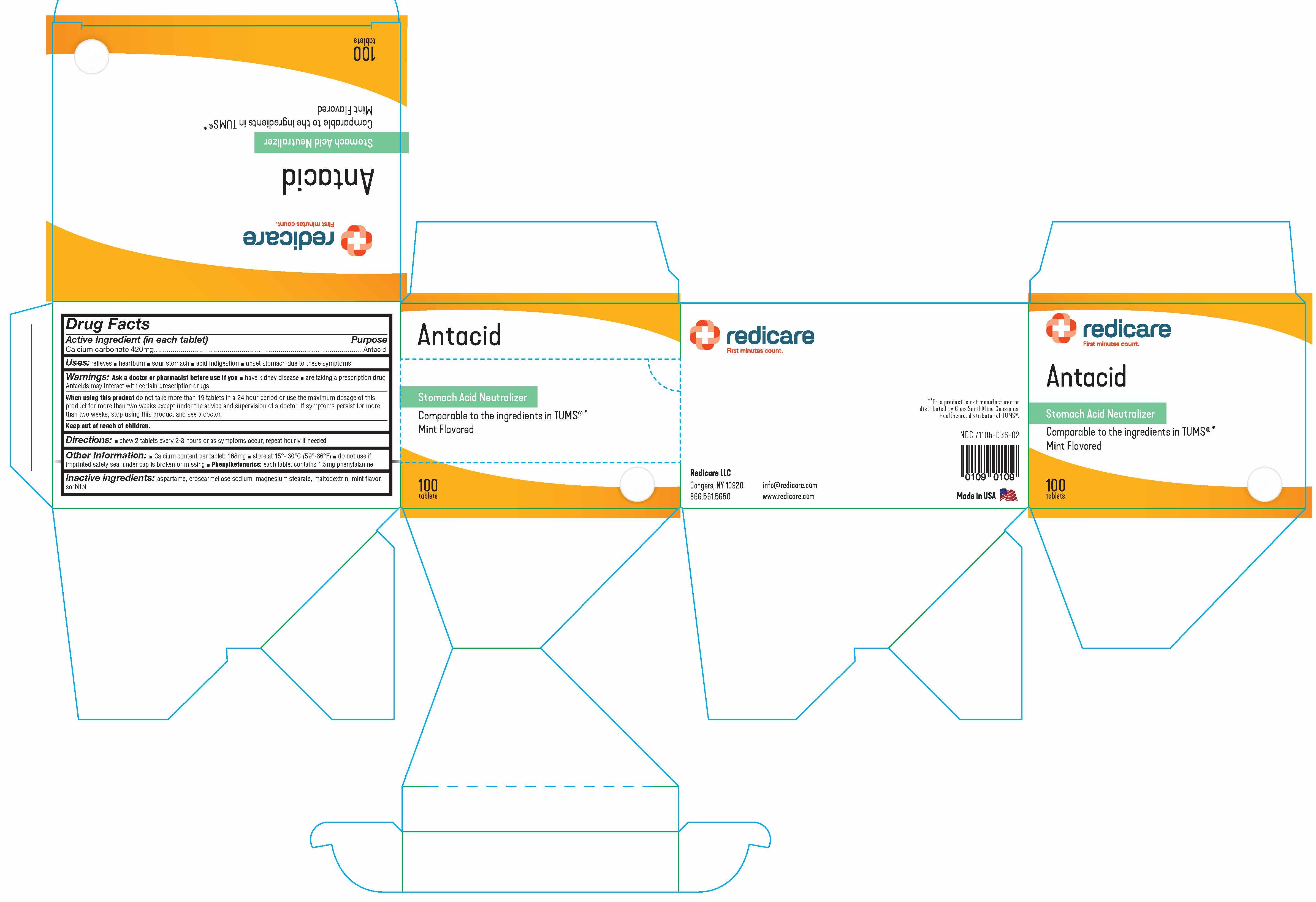 DRUG LABEL: Redicare Antacid Mint Flavored
NDC: 71105-036 | Form: TABLET, CHEWABLE
Manufacturer: Redicare LLC
Category: otc | Type: HUMAN OTC DRUG LABEL
Date: 20250304

ACTIVE INGREDIENTS: CALCIUM CARBONATE 420 mg/1 1
INACTIVE INGREDIENTS: MAGNESIUM STEARATE; ASPARTAME; CROSCARMELLOSE SODIUM; SORBITOL; MALTODEXTRIN

Active Ingredient (in each tablet)

Calcium carbonate 420mg

Purpose

Antacid

Uses:

relieves ■ heartburn ■ sour stomach ■ acid indigestion ■ upset stomach due to these symptoms

Warnings:

Ask a doctor or pharmacist before use if you

■ have kidney disease ■ are taking a prescription drug

Antacids may interact with certain prescription drugs

When using this product

do not take more than 19 tablets in a 24 hour period or use the maximum dosage of this product for more than two weeks except under the advice and supervision of a doctor. If symptoms persist for more than two weeks, stop using this product and see a doctor.

Directions:

■ chew 2 tablets every 2-3 hours or as symptoms occur, repeat hourly if needed

Other Information:

■ Calcium content per tablet: 168mg ■ store at 15°- 30°C (59°-86°F) ■ do not use if imprinted safety seal under cap is broken or missing ■ Phenylketonurics: each tablet contains 1.5mg phenylalanine

Inactive ingredients:

aspartame, croscarmellose sodium, magnesium stearate, maltodextrin, mint flavor, sorbitol